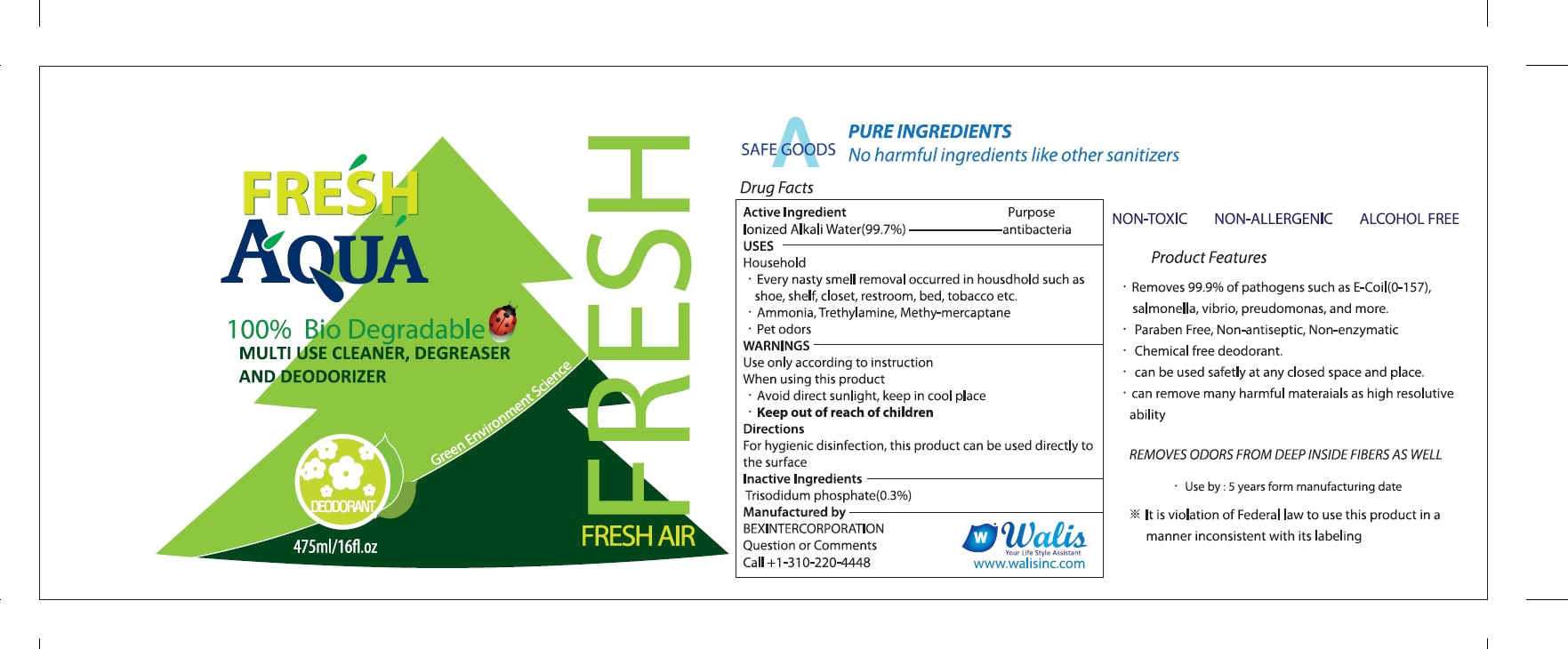 DRUG LABEL: FRESH AQUA
NDC: 70610-107 | Form: LIQUID
Manufacturer: KOTUKU INC.
Category: otc | Type: HUMAN OTC DRUG LABEL
Date: 20180907

ACTIVE INGREDIENTS: WATER 473.6 g/475 mL
INACTIVE INGREDIENTS: SODIUM PHOSPHATE, TRIBASIC, ANHYDROUS

FRESH AQUA